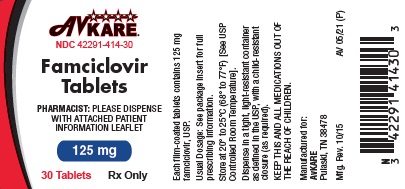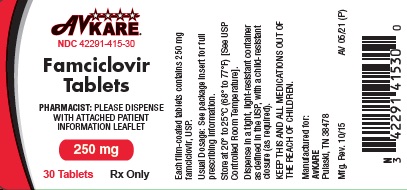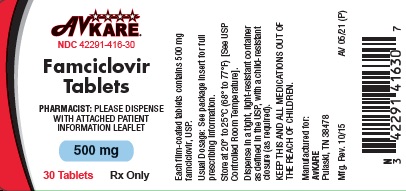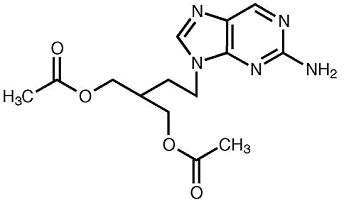 DRUG LABEL: Famciclovir
NDC: 42291-414 | Form: TABLET, FILM COATED
Manufacturer: AvKARE
Category: prescription | Type: HUMAN PRESCRIPTION DRUG LABEL
Date: 20260114

ACTIVE INGREDIENTS: FAMCICLOVIR 125 mg/1 1
INACTIVE INGREDIENTS: CROSCARMELLOSE SODIUM; HYDROXYPROPYL CELLULOSE, LOW SUBSTITUTED; HYPROMELLOSE 2910 (3 MPA.S); HYPROMELLOSE 2910 (6 MPA.S); HYPROMELLOSE 2910 (50 MPA.S); POLYDEXTROSE; POLYETHYLENE GLYCOL, UNSPECIFIED; SILICON DIOXIDE; CELLULOSE, MICROCRYSTALLINE; SODIUM STARCH GLYCOLATE TYPE A POTATO; SODIUM STEARYL FUMARATE; TITANIUM DIOXIDE; TRIACETIN

HIGHLIGHTS OF PRESCRIBING INFORMATION

Famciclovir Tablets
Rx only
These highlights do not include all the information needed to use FAMCICLOVIR TABLETS safely and effectively. See full prescribing information for FAMCICLOVIR TABLETS.
Initial U.S. Approval: 1994

1 INDICATIONS AND USAGE

Famciclovir tablets, a prodrug of penciclovir, are a deoxynucleoside analog DNA polymerase inhibitor indicated for:

Immunocompetent Adult Patients (1.1)

- Herpes labialis (cold sores)
  - Treatment of recurrent episodes
- Genital herpes
  - Treatment of recurrent episodes
  - Suppressive therapy of recurrent episodes
- Herpes zoster (shingles)

Human Immunodeficiency Virus (HIV)-Infected Adult Patients (1.2)

- Treatment of recurrent episodes of orolabial or genital herpes

Limitation of Use

The efficacy and safety of famciclovir tablets have not been established for:

- Patients with first episode of genital herpes
- Patients with ophthalmic zoster
- Immunocompromised patients other than for the treatment of recurrent episodes of orolabial or genital herpes in HIV-infected patients
- Black and African American patients with recurrent genital herpes

2 DOSAGE AND ADMINISTRATION

Immunocompetent Adult Patients (2.1)
Herpes labialis (cold sores) | 1500 mg as a single dose
Genital herpes
Treatment of recurrent episodes | 1000 mg twice daily for 1 day
Suppressive therapy | 250 mg twice daily
Herpes zoster (shingles) | 500 mg every 8 hours for 7 days
HIV-Infected Adult Patients (2.2)
Recurrent episodes of orolabial or genital herpes | 500 mg twice daily for 7 days

Patients with renal impairment: Adjust dose based on creatinine clearance. (2.3)

3 DOSAGE FORMS AND STRENGTHS

Tablets: 125 mg, 250 mg, 500 mg (3)

4 CONTRAINDICATIONS

Known hypersensitivity to the product, its components, or Denavir® (penciclovir cream). (4)

5 WARNINGS AND PRECAUTIONS

Acute renal failure: May occur in patients with underlying renal disease who receive higher than recommended doses of famciclovir for their level of renal function. Reduce dosage in patients with renal impairment. (2.3, 8.6)

6 ADVERSE REACTIONS

The most common adverse events reported in at least 1 indication by greater than 10% of adult patients are headache and nausea. (6.1)

To report SUSPECTED ADVERSE REACTIONS, contact AvKARE at 1-855-361-3993 or FDA at 1-800-FDA-1088 or www.fda.gov/medwatch.

7 DRUG INTERACTIONS

Probenecid: May increase penciclovir levels. Monitor for evidence of penciclovir toxicity. (7.2)

FULL PRESCRIBING INFORMATION

1 INDICATIONS AND USAGE

1.1 Immunocompetent Adult Patients

Herpes labialis (cold sores): Famciclovir tablets are indicated for the treatment of recurrent herpes labialis in adult patients.

Genital herpes:

Recurrent episodes: Famciclovir tablets are indicated for the treatment of recurrent episodes of genital herpes. The efficacy of famciclovir tablets when initiated more than 6 hours after onset of symptoms or lesions has not been established.

Suppressive therapy: Famciclovir tablets are indicated for chronic suppressive therapy of recurrent episodes of genital herpes in adult patients. The efficacy and safety of famciclovir tablets for the suppression of recurrent genital herpes beyond 1 year have not been established.

Herpes zoster (shingles): Famciclovir tablets are indicated for the treatment of herpes zoster in adult patients. The efficacy of famciclovir tablets when initiated more than 72 hours after onset of rash has not been established.

1.2 HIV-Infected Adult Patients

Recurrent orolabial or genital herpes: Famciclovir tablets are indicated for the treatment of recurrent episodes of orolabial or genital herpes in HIV-infected adults. The efficacy of famciclovir tablets when initiated more than 48 hours after onset of symptoms or lesions has not been established.

Limitation of Use

The efficacy and safety of famciclovir tablets have not been established for:

- Patients with first episode of genital herpes
- Patients with ophthalmic zoster
- Immunocompromised patients other than for the treatment of recurrent orolabial or genital herpes in HIV-infected patients
- Black and African American patients with recurrent genital herpes

2 DOSAGE AND ADMINISTRATION

Famciclovir tablets may be taken with or without food.

2.1 Dosing Recommendation in Immunocompetent Adult Patients

Herpes labialis (cold sores): The recommended dosage of famciclovir tablets for the treatment of recurrent herpes labialis is 1500 mg as a single dose. Therapy should be initiated at the first sign or symptom of herpes labialis (e.g., tingling, itching, burning, pain, or lesion).

Genital herpes:

Recurrent episodes: The recommended dosage of famciclovir tablets for the treatment of recurrent episodes of genital herpes is 1000 mg twice daily for 1 day. Therapy should be initiated at the first sign or symptom of a recurrent episode (e.g., tingling, itching, burning, pain, or lesion).

Suppressive therapy: The recommended dosage of famciclovir tablets for chronic suppressive therapy of recurrent episodes of genital herpes is 250 mg twice daily.

Herpes zoster (shingles): The recommended dosage of famciclovir tablets for the treatment of herpes zoster is 500 mg every 8 hours for 7 days. Therapy should be initiated as soon as herpes zoster is diagnosed.

2.2 Dosing Recommendation in HIV-Infected Adult Patients

Recurrent orolabial or genital herpes: The recommended dosage of famciclovir tablets for the treatment of recurrent orolabial or genital herpes in HIV-infected patients is 500 mg twice daily for 7 days. Therapy should be initiated at the first sign or symptom of a recurrent episode (e.g., tingling, itching, burning, pain, or lesion).

2.3 Dosing Recommendation in Patients with Renal Impairment

Dosage recommendations for adult patients with renal impairment are provided in Table 1 [see Use in Specific Populations (8.6), Clinical Pharmacology (12.3) ] .

Table 1: Dosage Recommendations for Adult Patients with Renal Impairment
Indication and Normal Dosage Regimen | Creatinine Clearance (mL/min) | Adjusted Dosage Regimen Dose (mg) | Dosing Interval
Single-Day Dosing Regimens
Recurrent Genital Herpes
1000 mg every 12 hours for 1 day | ≥60 | 1000 | every 12 hours for 1 day
 | 40 to 59 | 500 | every 12 hours for 1 day
 | 20 to 39 | 500 | single dose
 | <20 | 250 | single dose
 | HD [Hemodialysis] | 250 | single dose following dialysis
Recurrent Herpes Labialis
1500 mg single dose | ≥60 | 1500 | single dose
 | 40 to 59 | 750 | single dose
 | 20 to 39 | 500 | single dose
 | <20 | 250 | single dose
 | HD | 250 | single dose following dialysis
Multiple-Day Dosing Regimens
Herpes Zoster
500 mg every 8 hours | ≥60 | 500 | every 8 hours
 | 40 to 59 | 500 | every 12 hours
 | 20 to 39 | 500 | every 24 hours
 | <20 | 250 | every 24 hours
 | HD | 250 | following each dialysis
Suppression of Recurrent; Genital Herpes
250 mg every 12 hours | ≥40 | 250 | every 12 hours
 | 20 to 39 | 125 | every 12 hours
 | <20 | 125 | every 24 hours
 | HD | 125 | following each dialysis
Recurrent Orolabial; or Genital Herpes; in HIV-Infected Patients
500 mg every 12 hours | ≥40 | 500 | every 12 hours
 | 20 to 39 | 500 | every 24 hours
 | <20 | 250 | every 24 hours
 | HD | 250 | following each dialysis

3 DOSAGE FORMS AND STRENGTHS

Famciclovir Tablets are available in three strengths:

- 125 mg: White, round, film-coated, unscored tablets, debossed with “8117” on one side and “93” on the other side
- 250 mg: White, round, film-coated, unscored tablets, debossed with “8118” on one side and “93” on the other side
- 500 mg: White, capsule-shaped, film-coated, unscored tablets, debossed with “8119” on one side and “93” on the other side

4 CONTRAINDICATIONS

Famciclovir is contraindicated in patients with known hypersensitivity to the product, its components, or Denavir® (penciclovir cream).

5 WARNINGS AND PRECAUTIONS

5.1 Acute Renal Failure

Cases of acute renal failure have been reported in patients with underlying renal disease who have received inappropriately high doses of famciclovir for their level of renal function. Dosage reduction is recommended when administering famciclovir to patients with renal impairment [see Dosage and Administration (2.3), Use in Specific Populations (8.6) ] .

6 ADVERSE REACTIONS

Acute renal failure is discussed in greater detail in other sections of the label [see Warnings and Precautions (5) ] .

The most common adverse events reported in at least 1 indication by greater than 10% of adult patients treated with famciclovir are headache and nausea.

6.1 Clinical Trials Experience in Adult Patients

Because clinical trials are conducted under widely varying conditions, adverse reaction rates observed in the clinical trials of a drug cannot be directly compared with rates in the clinical trials of another drug and may not reflect the rates observed in practice.

Immunocompetent patients: The safety of famciclovir has been evaluated in active- and placebo-controlled clinical studies involving 816 famciclovir-treated patients with herpes zoster (famciclovir, 250 mg three times daily to 750 mg three times daily); 163 famciclovir-treated patients with recurrent genital herpes (famciclovir, 1000 mg twice daily); 1,197 patients with recurrent genital herpes treated with famciclovir as suppressive therapy (125 mg once daily to 250 mg three times daily) of which 570 patients received famciclovir (open-labeled and/or double-blind) for at least 10 months; and 447 famciclovir-treated patients with herpes labialis (famciclovir, 1500 mg once daily or 750 mg twice daily). Table 2 lists selected adverse events.

Table 2: Selected Adverse Events (all grades and without regard to causality) Reported by Greater than or Equal to 2% of Patients in Placebo-Controlled Famciclovir Trials [Patients may have entered into more than one clinical trial.]
Incidence
Events | Herpes Zoster [7 days of treatment] |  | Recurrent Genital Herpes [1 day of treatment] |  | Genital Herpes- Supression [daily treatment] |  | Herpes Labialis
Events | Famciclovir; (n=273); % | Placebo; (n=146); % | Famciclovir; (n=163); % | Placebo; (n=166); % | Famciclovir; (n=458); % | Placebo; (n=63); % | Famciclovir; (n=447); % | Placebo; (n=254); %
Nervous System
Headache | 22.7 | 17.8 | 13.5 | 5.4 | 39.3 | 42.9 | 8.5 | 6.7
Paresthesia | 2.6 | 0.0 | 0.0 | 0.0 | 0.9 | 0.0 | 0.0 | 0.0
Migraine | 0.7 | 0.7 | 0.6 | 0.6 | 3.1 | 0.0 | 0.2 | 0.0
Gastrointestinal
Nausea | 12.5 | 11.6 | 2.5 | 3.6 | 7.2 | 9.5 | 2.2 | 3.9
Diarrhea | 7.7 | 4.8 | 4.9 | 1.2 | 9.0 | 9.5 | 1.6 | 0.8
Vomiting | 4.8 | 3.4 | 1.2 | 0.6 | 3.1 | 1.6 | 0.7 | 0.0
Flatulence | 1.5 | 0.7 | 0.6 | 0.0 | 4.8 | 1.6 | 0.2 | 0.0
Abdominal Pain | 1.1 | 3.4 | 0.0 | 1.2 | 7.9 | 7.9 | 0.2 | 0.4
Body as a Whole
Fatigue | 4.4 | 3.4 | 0.6 | 0.0 | 4.8 | 3.2 | 1.6 | 0.4
Skin and Appendages
Pruritus | 3.7 | 2.7 | 0.0 | 0.6 | 2.2 | 0.0 | 0.0 | 0.0
Rash | 0.4 | 0.7 | 0.0 | 0.0 | 3.3 | 1.6 | 0.0 | 0.0
Reproductive (Female)
Dysmenorrhea | 0.0 | 0.7 | 1.8 | 0.6 | 7.6 | 6.3 | 0.4 | 0.0

Table 3 lists selected laboratory abnormalities in genital herpes suppression trials.

Table 3: Selected Laboratory Abnormalities in Genital Herpes Suppression Studies [Percentage of patients with laboratory abnormalities that were increased or decreased from baseline and were outside of specified ranges.]
Parameter | Famciclovir; (n=660) [n values represent the minimum number of patients assessed for each laboratory parameter.] % | Placebo; (n=210) %
Anemia (<0.8 x NRL) | 0.1 | 0.0
Leukopenia (<0.75 x NRL) | 1.3 | 0.9
Neutropenia (<0.8 x NRL) | 3.2 | 1.5
AST (SGOT) (>2 x NRH) | 2.3 | 1.2
ALT (SGPT) (>2 x NRH) | 3.2 | 1.5
Total Bilirubin (>1.5 x NRH) | 1.9 | 1.2
Serum Creatinine (>1.5 x NRH) | 0.2 | 0.3
Amylase (>1.5 x NRH) | 1.5 | 1.9
Lipase (>1.5 x NRH) | 4.9 | 4.7

NRH = Normal Range High.
NRL = Normal Range Low.

HIV-infected patients: In HIV-infected patients, the most frequently reported adverse events for famciclovir (500 mg twice daily; n=150) and acyclovir (400 mg, 5x/day; n=143), respectively, were headache (17% vs. 15%), nausea (11% vs. 13%), diarrhea (7% vs. 11%), vomiting (5% vs. 4%), fatigue (4% vs. 2%), and abdominal pain (3% vs. 6%).

6.2 Postmarketing Experience

The adverse events listed below have been reported during post-approval use of famciclovir. Because these events are reported voluntarily from a population of uncertain size, it is not always possible to reliably estimate their frequency or establish a causal relationship to drug exposure:

Blood and lymphatic system disorders: Thrombocytopenia

Hepatobiliary disorders: Abnormal liver function tests, cholestatic jaundice

Immune system disorders: Anaphylactic shock, anaphylactic reaction

Nervous system disorders: Dizziness, somnolence, seizure

Psychiatric disorders: Confusion (including delirium, disorientation, and confusional state occurring predominantly in the elderly), hallucinations

Skin and subcutaneous tissue disorders: Urticaria, erythema multiforme, Stevens-Johnson syndrome, toxic epidermal necrolysis, angioedema (e.g., face, eyelid, periorbital, and pharyngeal edema), hypersensitivity vasculitis

Cardiac disorders: Palpitations

To report SUSPECTED ADVERSE REACTIONS contact AvKARE at 1-855-361-3993; email drugsafety@avkare.com; or FDA at 1-800-FDA-1088 or www.fda.gov/medwatch.

7 DRUG INTERACTIONS

7.1 Potential for Famciclovir to Affect Other Drugs

The steady-state pharmacokinetics of digoxin were not altered by concomitant administration of multiple doses of famciclovir (500 mg three times daily). No clinically significant effect on the pharmacokinetics of zidovudine, its metabolite zidovudine glucuronide, or emtricitabine was observed following a single oral dose of 500 mg famciclovir coadministered with zidovudine or emtricitabine.

An in vitro study using human liver microsomes suggests that famciclovir is not an inhibitor of CYP3A4 enzymes.

7.2 Potential for Other Drugs to Affect Penciclovir

No clinically significant alterations in penciclovir pharmacokinetics were observed following single-dose administration of 500 mg famciclovir after pretreatment with multiple doses of allopurinol, cimetidine, theophylline, zidovudine, promethazine, when given shortly after an antacid (magnesium and aluminum hydroxide), or concomitantly with emtricitabine. No clinically significant effect on penciclovir pharmacokinetics was observed following multiple-dose (three times daily) administration of famciclovir (500 mg) with multiple doses of digoxin.

Concurrent use with probenecid or other drugs significantly eliminated by active renal tubular secretion may result in increased plasma concentrations of penciclovir.

The conversion of 6-deoxy penciclovir to penciclovir is catalyzed by aldehyde oxidase. Interactions with other drugs metabolized by this enzyme and/or inhibiting this enzyme could potentially occur. Clinical interaction studies of famciclovir with cimetidine and promethazine, in vitro inhibitors of aldehyde oxidase, did not show relevant effects on the formation of penciclovir. Raloxifene, a potent aldehyde oxidase inhibitor in vitro, could decrease the formation of penciclovir. However, a clinical drug-drug interaction study to determine the magnitude of interaction between penciclovir and raloxifene has not been conducted.

8 USE IN SPECIFIC POPULATIONS

8.1 Pregnancy

Risk Summary

Available data from pharmacovigilance reports with famciclovir use in pregnant women have not identified a drug-associated risk of major birth defects, miscarriage or adverse maternal or fetal outcomes. There are risks to the fetus associated with untreated herpes simplex virus during pregnancy (see Clinical Considerations). After oral administration, famciclovir (prodrug) is converted to penciclovir (active drug). In animal reproduction studies with famciclovir, no evidence of adverse developmental outcomes was observed at systemic exposures of penciclovir (AUC) slightly higher than those at the maximum recommended human dose (MRHD) of famciclovir (see Data).

The estimated background risk of major birth defects and miscarriage for the indicated population is unknown. All pregnancies have a background risk of birth defect, loss, or other adverse outcomes. In the U.S. general population, the estimated background risk of major birth defects and miscarriage in clinically recognized pregnancies is 2 to 4% and 15 to 20%, respectively.

Clinical Considerations

Disease-associated maternal and/or embryo-fetal risk

The risk of neonatal herpes infection varies from 30% to 50% for genital herpes simplex virus (HSV) infections that occur in late pregnancy (third trimester), whereas in early pregnancy, infection carries a risk of about 1%. A primary herpes outbreak during the first trimester of pregnancy has been associated with neonatal chorioretinitis, microcephaly and, in rare cases, skin lesions. In very rare cases, transplacental transmission can occur resulting in congenital infection, including microcephaly, hepatosplenomegaly, intrauterine growth restriction and stillbirth. Co-infection with HSV increases the risk of perinatal HIV transmission in women who had a clinical diagnosis of genital herpes during pregnancy.

Data

Animal Data

Famciclovir was administered orally to pregnant rats and rabbits (up to 1000 mg/kg/day) on gestation Day(s) 6 to 15, and to rats on gestation Day 15 to lactation/post-partum Day 25. No adverse effects on embryo-fetal (rats and rabbits) or pre/post-natal (rats) development were observed up to the highest dose tested. During organogenesis, systemic exposures of penciclovir (active metabolite) were 3.4 times (rats) and 1.6 times (rabbits) the human systemic exposure of penciclovir based on AUC at the MRHD.

8.2 Lactation

Risk Summary

There are no data on the presence of famciclovir (prodrug) or penciclovir (active drug) in human milk, the effects on the breastfed infant, or the effects on milk production. Animal data indicate that penciclovir is present in the milk of lactating rats (see Data). The developmental and health benefits of breastfeeding should be considered along with the mother’s clinical need for famciclovir and any potential adverse effects on the breastfed infant from famciclovir or from the underlying maternal condition.

Data

Penciclovir was the primary drug-related component excreted into the milk of lactating rats following a single oral dose of 40 mg per kg on lactation Day 12, with milk concentrations of up to approximately 8 times that of maternal plasma concentrations observed 0.5 hours postdose.

8.3 Females and Males of Reproductive Potential

Infertility

Decreased fertility, due to testicular toxicity, was observed in male animals following repeated administration of famciclovir or penciclovir [see Nonclinical Toxicology (13.1)] .

In two placebo-controlled studies, 130 men with a history of recurrent genital herpes received either oral famciclovir (250 mg twice daily; n=66) or placebo (n=64) therapy for 18 weeks. The men were otherwise healthy and had a normal sperm profile prior to treatment. There was no evidence of significant effects on sperm count, motility or morphology during famciclovir treatment or during an 8-week follow-up.

8.4 Pediatric Use

The efficacy of famciclovir has not been established in pediatric patients. The pharmacokinetic profile and safety of famciclovir (experimental granules mixed with OraSweet® or tablets) were studied in 3 open-label studies.

Study 1 was a single-dose pharmacokinetic and safety study in infants 1 month to less than 1 year of age who had an active herpes simplex virus (HSV) infection or who were at risk for HSV infection. Eighteen subjects were enrolled and received a single dose of famciclovir experimental granules mixed with OraSweet based on the patient’s body weight (doses ranged from 25 mg to 175 mg). These doses were selected to provide penciclovir systemic exposures similar to the penciclovir systemic exposures observed in adults after administration of 500 mg famciclovir. The efficacy and safety of famciclovir have not been established as suppressive therapy in infants following neonatal HSV infections. In addition, the efficacy cannot be extrapolated from adults to infants because there is no similar disease in adults. Therefore, famciclovir is not recommended in infants.

Study 2 was an open-label, single-dose pharmacokinetic, multiple-dose safety study of famciclovir experimental granules mixed with OraSweet in children 1 to less than 12 years of age with clinically suspected HSV or varicella zoster virus (VZV) infection. Fifty-one subjects were enrolled in the pharmacokinetic part of the study and received a single body weight adjusted dose of famciclovir (doses ranged from 125 mg to 500 mg). These doses were selected to provide penciclovir systemic exposures similar to the penciclovir systemic exposures observed in adults after administration of 500 mg famciclovir. Based on the pharmacokinetic data observed with these doses in children, a new weight-based dosing algorithm was designed and used in the multiple-dose safety part of the study. Pharmacokinetic data were not obtained with the revised weight-based dosing algorithm.

A total of 100 patients were enrolled in the multiple-dose safety part of the study; 47 subjects with active or latent HSV infection and 53 subjects with chickenpox. Patients with active or latent HSV infection received famciclovir twice a day for 7 days. The daily dose of famciclovir ranged from 150 mg to 500 mg twice daily depending on the patient’s body weight. Patients with chickenpox received famciclovir three times daily for 7 days. The daily dose of famciclovir ranged from 150 mg to 500 mg three times daily depending on the patient’s body weight. The clinical adverse events and laboratory test abnormalities observed in this study were similar to these seen in adults. The available data are insufficient to support the use of famciclovir for the treatment of children 1 to less than 12 years of age with chickenpox or infections due to HSV for the following reasons:

Chickenpox: The efficacy of famciclovir for the treatment of chickenpox has not been established in either pediatric or adult patients. Famciclovir is approved for the treatment of herpes zoster in adult patients. However, extrapolation of efficacy data from adults with herpes zoster to children with chickenpox would not be appropriate. Although chickenpox and herpes zoster are caused by the same virus, the diseases are different.

Genital herpes: Clinical information on genital herpes in children is limited. Therefore, efficacy data from adults cannot be extrapolated to this population. Further, famciclovir has not been studied in children 1 to less than 12 years of age with recurrent genital herpes. None of the children in Study 2 had genital herpes.

Herpes labialis: There are no pharmacokinetic and safety data in children 1 to less than 12 years of age to support a famciclovir dose that provides penciclovir systemic exposures comparable to the penciclovir systemic exposures in adults after a single dose administration of 1500 mg. Moreover, no efficacy data have been obtained in children 1 to less than 12 years of age with recurrent herpes labialis.

Study 3 was an open-label, single-arm study to evaluate the pharmacokinetics, safety, and antiviral activity of a single 1500 mg dose (three 500 mg tablets) of famciclovir in children 12 to less than 18 years of age with recurrent herpes labialis. A total of 53 subjects were enrolled in the study; 10 subjects in the pharmacokinetic part of the study and 43 subjects in the non-pharmacokinetic part of the study. All enrolled subjects weighed greater than or equal to 40 kg. The 43 subjects enrolled in the non-pharmacokinetic part of the study had active recurrent herpes labialis and received a single 1500 mg dose of famciclovir within 24 hours after the onset of symptoms (median time to treatment initiation was 21 hours). The safety profile of famciclovir observed in this study was similar to that seen in adults. The median time to healing of patients with non-aborted lesions was 5.9 days.

In a phase 3 trial in adults in which patients received a single 1500 mg dose of famciclovir or placebo, the median time to healing among patients with non-aborted lesions was 4.4 days in the famciclovir 1500 mg single-dose group and 6.2 days in the placebo group. Of note, in the adult study treatment was initiated by patients within 1 hour after the onset of symptoms [see Clinical Studies (14.1) ]. Based on the efficacy results in Study 3, famciclovir is not recommended in children 12 to less than 18 years of age with recurrent herpes labialis.

8.5 Geriatric Use

Of 816 patients with herpes zoster in clinical studies who were treated with famciclovir, 248 (30.4%) were greater than or equal to 65 years of age and 103 (13%) were greater than or equal to 75 years of age. No overall differences were observed in the incidence or types of adverse events between younger and older patients. Of 610 patients with recurrent herpes simplex (type 1 or type 2) in clinical studies who were treated with famciclovir, 26 (4.3%) were greater than 65 years of age and 7 (1.1%) were greater than 75 years of age. Clinical studies of famciclovir in patients with recurrent genital herpes did not include sufficient numbers of subjects aged 65 years and over to determine whether they respond differently compared to younger subjects.

No famciclovir dosage adjustment based on age is recommended unless renal function is impaired [see Dosage and Administration (2.3), Clinical Pharmacology (12.3) ]. In general, appropriate caution should be exercised in the administration and monitoring of famciclovir in elderly patients reflecting the greater frequency of decreased renal function and concomitant use of other drugs.

8.6 Patients with Renal Impairment

Apparent plasma clearance, renal clearance, and the plasma-elimination rate constant of penciclovir decreased linearly with reductions in renal function. After the administration of a single 500 mg famciclovir oral dose (n=27) to healthy volunteers and to volunteers with varying degrees of renal impairment (CLCR ranged from 6.4 to 138.8 mL/min), the following results were obtained (Table 4):

Table 4: Pharmacokinetic Parameters of Penciclovir in Subjects with Different Degrees of Renal Impairment
Parameter; (mean ± S.D.) | CLCR [CL CR is measured creatinine clearance.] ≥60; (mL/min); (n=15) | CLCR 40 to 59; (mL/min); (n=5) | CLCR 20 to 39; (mL/min); (n=4) | CLCR <20; (mL/min); (n=3)
CLCR (mL/min) | 88.1 ± 20.6 | 49.3 ± 5.9 | 26.5 ± 5.3 | 12.7 ± 5.9
CLR (L/hr) | 30.1 ± 10.6 | 13 ± 1.3 [n=4.] | 4.2 ± 0.9 | 1.6 ± 1.0
CL/F [CL/F consists of bioavailability factor and famciclovir to penciclovir conversion factor.] (L/hr) | 66.9 ± 27.5 | 27.3 ± 2.8 | 12.8 ± 1.3 | 5.8 ± 2.8
Half-life (hr) | 2.3 ± 0.5 | 3.4 ± 0.7 | 6.2 ± 1.6 | 13.4 ± 10.2

In a multiple-dose study of famciclovir conducted in subjects with varying degrees of renal impairment (n=18), the pharmacokinetics of penciclovir were comparable to those after single doses.

A dosage adjustment is recommended for patients with renal impairment [see Dosage and Administration (2.3) ] .

8.7 Patients with Hepatic Impairment

Mild or moderate hepatic impairment (chronic hepatitis [n=6], chronic ethanol abuse [n=8], or primary biliary cirrhosis [n=1]) had no effect on the extent of availability (AUC) of penciclovir following a single dose of 500 mg famciclovir. However, there was a 44% decrease in penciclovir mean maximum plasma concentration (Cmax) and the time to maximum plasma concentration (tmax) was increased by 0.75 hours in patients with hepatic impairment compared to normal volunteers. No dosage adjustment is recommended for patients with mild or moderate hepatic impairment. The pharmacokinetics of penciclovir has not been evaluated in patients with severe hepatic impairment. Conversion of famciclovir to the active metabolite penciclovir may be impaired in these patients resulting in a lower penciclovir plasma concentrations, and thus possibly a decrease of efficacy of famciclovir [see Clinical Pharmacology (12) ].

8.8 Black and African American Patients

In a randomized, double-blind, placebo-controlled trial conducted in 304 immunocompetent black and African American adults with recurrent genital herpes there was no difference in median time to healing between patients receiving famciclovir or placebo. In general, the adverse reaction profile was similar to that observed in other famciclovir clinical trials for adult patients [see Adverse Reactions (6.1) ]. The relevance of these study results to other indications in black and African American patients is unknown [see Clinical Studies (14.2) ].

10 OVERDOSAGE

Appropriate symptomatic and supportive therapy should be given. Penciclovir is removed by hemodialysis.

11 DESCRIPTION

Famciclovir Tablets contain famciclovir, USP, an orally administered prodrug of the antiviral agent penciclovir. Chemically, famciclovir, USP is known as 2-[2-(2-amino-9 H-purin-9-yl)ethyl]-1,3-propanediol diacetate. It is a synthetic acyclic guanine derivative and has the following structure:

C14H19N5O4 M.W. 321.3

Famciclovir, USP is a white to pale yellow solid. It is freely soluble in acetone and methanol, and sparingly soluble in ethanol and isopropanol. At 25°C famciclovir, USP is freely soluble (greater than 25% w/v) in water initially, but rapidly precipitates as the sparingly soluble (2% to 3% w/v) monohydrate. Famciclovir, USP is not hygroscopic below 85% relative humidity. Partition coefficients are: octanol/water (pH 4.8) P = 1.09 and octanol/phosphate buffer (pH 7.4) P = 2.08.

Each white, film-coated tablet contains famciclovir, USP. The 125 mg and 250 mg tablets are round; the 500 mg tablets are capsule-shaped. Inactive ingredients consist of croscarmellose sodium, hydroxypropyl cellulose, hypromellose, polydextrose, polyethylene glycol, silicified microcrystalline cellulose, sodium starch glycolate, sodium stearyl fumarate, titanium dioxide, and triacetin.

12 CLINICAL PHARMACOLOGY

12.1 Mechanism of Action

Famciclovir is an orally administered prodrug of the anti-alpha herpes viral agent penciclovir [see Microbiology (12.4) ] .

12.3 Pharmacokinetics

Famciclovir is the diacetyl 6-deoxy analog of the active antiviral compound penciclovir. Following oral administration famciclovir undergoes rapid and extensive metabolism to penciclovir and little or no famciclovir is detected in plasma or urine. Penciclovir is predominantly eliminated unchanged by the kidney. Therefore, the dose of famciclovir needs to be adjusted in patients with different degrees of renal impairment [see Dosage and Administration (2.3) ].

Pharmacokinetics in adults:

Absorption and Bioavailability: The absolute bioavailability of penciclovir is 77 ± 8% as determined following the administration of a 500 mg famciclovir oral dose and a 400 mg penciclovir intravenous dose to 12 healthy male subjects.

Penciclovir concentrations increased in proportion to dose over a famciclovir dose range of 125 mg to 1000 mg administered as a single dose. Table 5 shows the mean pharmacokinetic parameters of penciclovir after single administration of famciclovir to healthy male volunteers.

Table 5: Mean Pharmacokinetic Parameters of Penciclovir in Healthy Adult Subjects [Based on pharmacokinetic data from 17 studies.]
Dose | AUC (0-inf) [AUC (0-inf) (mcg hr/mL) = area under the plasma concentration-time profile extrapolated to infinity.] (mcg hr/mL) | Cmax [C max (mcg/mL) = maximum observed plasma concentration.] (mcg/mL) | Tmax [t max (h) = time to C max.] (h)
125 mg | 2.24 | 0.8 | 0.9
250 mg | 4.48 | 1.6 | 0.9
500 mg | 8.95 | 3.3 | 0.9
1000 mg | 17.9 | 6.6 | 0.9

Following oral single-dose administration of 500 mg famciclovir to 7 patients with herpes zoster, the AUC (mean ± SD), Cmax, and tmax were 12.1±1.7 mcg hr/mL, 4.0±0.7 mcg/mL, and 0.7±0.2 hours, respectively. The AUC of penciclovir was approximately 35% greater in patients with herpes zoster as compared to healthy volunteers. Some of this difference may be due to differences in renal function between the 2 groups.

There is no accumulation of penciclovir after the administration of 500 mg famciclovir three times daily for 7 days.

Penciclovir Cmax decreased approximately 50% and tmax was delayed by 1.5 hours when a capsule formulation of famciclovir was administered with food (nutritional content was approximately 910 Kcal and 26% fat). There was no effect on the extent of availability (AUC) of penciclovir. There was an 18% decrease in Cmax and a delay in tmax of about 1 hour when famciclovir was given 2 hours after a meal as compared to its administration 2 hours before a meal. Because there was no effect on the extent of systemic availability of penciclovir, famciclovir can be taken without regard to meals.

Distribution: The volume of distribution (Vdβ) was 1.08±0.17 L/kg in 12 healthy male subjects following a single intravenous dose of penciclovir at 400 mg administered as a 1-hour intravenous infusion. Penciclovir is less than 20% bound to plasma proteins over the concentration range of 0.1 to 20 mcg/mL. The blood/plasma ratio of penciclovir is approximately

1.

Metabolism: Following oral administration, famciclovir is deacetylated and oxidized to form penciclovir. Metabolites that are inactive include 6-deoxy penciclovir, monoacetylated penciclovir, and 6-deoxy monoacetylated penciclovir (5%, less than 0.5% and less than 0.5% of the dose in the urine, respectively). Little or no famciclovir is detected in plasma or urine. An in vitro study using human liver microsomes demonstrated that cytochrome P450 does not play an important role in famciclovir metabolism. The conversion of 6-deoxy penciclovir to penciclovir is catalyzed by aldehyde oxidase. Cimetidine and promethazine, in vitro inhibitors of aldehyde oxidase, did not show relevant effects on the formation of penciclovir in vivo [see Drug Interactions (7.2) ].

Elimination: Approximately 94% of administered radioactivity was recovered in urine over 24 hours (83% of the dose was excreted in the first 6 hours) after the administration of 5 mg/kg radiolabeled penciclovir as a 1-hour infusion to 3 healthy male volunteers. Penciclovir accounted for 91% of the radioactivity excreted in the urine.

Following the oral administration of a single 500 mg dose of radiolabeled famciclovir to 3 healthy male volunteers, 73% and 27% of administered radioactivity were recovered in urine and feces over 72 hours, respectively. Penciclovir accounted for 82% and 6-deoxy penciclovir accounted for 7% of the radioactivity excreted in the urine. Approximately 60% of the administered radiolabeled dose was collected in urine in the first 6 hours.

After intravenous administration of penciclovir in 48 healthy male volunteers, mean ± SD total plasma clearance of penciclovir was 36.6±6.3 L/hr (0.48±0.09 L/hr/kg). Penciclovir renal clearance accounted for 74.5±8.8% of total plasma clearance.

Renal clearance of penciclovir following the oral administration of a single 500 mg dose of famciclovir to 109 healthy male volunteers was 27.7±7.6 L/hr. Active tubular secretion contributes to the renal elimination of penciclovir.

The plasma elimination half-life of penciclovir was 2.0±0.3 hours after intravenous administration of penciclovir to 48 healthy male volunteers and 2.3±0.4 hours after oral administration of 500 mg famciclovir to 124 healthy male volunteers. The half-life in 17 patients with herpes zoster was 2.8±1.0 hours and 2.7±1.0 hours after single and repeated doses, respectively.

Special populations:

Geriatric patients: Based on cross study comparison, penciclovir AUC was 40% higher and penciclovir renal clearance was 22% lower in elderly subjects (n=18, age 65 to 79 years) as compared with younger subjects. Some of this difference may be due to differences in renal function between the 2 groups. No famciclovir dosage adjustment based on age is recommended unless renal function is impaired [see Dosage and Administration (2.3), Use in Specific Populations (8.5) ] .

Patients with renal impairment: In subjects with varying degrees of renal impairment, apparent plasma clearance, renal clearance, and the plasma-elimination rate constant of penciclovir decreased linearly with reductions in renal function, after both single and repeated dosing [see Use in Specific Populations (8.6) ] . A dosage adjustment is recommended for patients with renal impairment [see Dosage and Administration (2.3) ].

Patients with hepatic impairment: Mild or moderate hepatic impairment had no effect on the extent of availability (AUC) of penciclovir [see Use in Specific Populations (8.7) ]. No dosage adjustment is recommended for patients with mild or moderate hepatic impairment. The effect of severe hepatic impairment on the pharmacokinetics of penciclovir has not been evaluated.

HIV-infected patients: Following oral administration of a single dose of 500 mg famciclovir to HIV-positive patients, the pharmacokinetic parameters of penciclovir were comparable to those observed in healthy subjects.

Gender: The pharmacokinetics of penciclovir were evaluated in 18 healthy male and 18 healthy female volunteers after single-dose oral administration of 500 mg famciclovir. AUC of penciclovir was 9.3±1.9 mcg hr/mL and 11.1±2.1 mcg hr/mL in males and females, respectively. Penciclovir renal clearance was 28.5±8.9 L/hr and 21.8±4.3 L/hr, respectively. These differences were attributed to differences in renal function between the 2 groups. No famciclovir dosage adjustment based on gender is recommended.

Race: A retrospective evaluation was performed to compare the pharmacokinetic parameters obtained in black and Caucasian subjects after single and repeat once-daily, twice-daily, or three times-daily administration of famciclovir 500 mg. Data from a study in healthy volunteers (single dose), a study in subjects with varying degrees of renal impairment (single and repeat dose) and a study in subjects with hepatic impairment (single dose) did not indicate any significant differences in the pharmacokinetics of penciclovir between black and Caucasian subjects.

12.4 Microbiology

Mechanism of action: Famciclovir is a prodrug of penciclovir, which has demonstrated inhibitory activity against herpes simplex virus types 1 (HSV-1) and 2 (HSV-2) and varicella zoster virus (VZV). In cells infected with HSV-1, HSV-2 or VZV, the viral thymidine kinase phosphorylates penciclovir to a monophosphate form that, in turn, is converted by cellular kinases to the active form penciclovir triphosphate. Biochemical studies demonstrate that penciclovir triphosphate inhibits HSV-2 DNA polymerase competitively with deoxyguanosine triphosphate. Consequently, α-herpes viral DNA synthesis and, therefore, replication are selectively inhibited. Penciclovir triphosphate has an intracellular half-life of 10 hours in HSV-1-, 20 hours in HSV-2- and 7 hours in VZV-infected cells grown in culture. However, the clinical significance of the intracellular half-life is unknown.

Antiviral activity: In cell culture studies, penciclovir has antiviral activity against the following herpes viruses: HSV-1, HSV-2 and VZV. The antiviral activity of penciclovir against wild type strains grown on human foreskin fibroblasts was assessed with a plaque reduction assay and staining with crystal violet 3 days post-infection for HSV and 10 days postinfection for VZV. The median EC50 values of penciclovir against laboratory and clinical isolates of HSV-1, HSV-2, and VZV were 2 μM (range 1.2 to 2.4 μM, n=7), 2.6 μM (range 1.6 to 11 μM, n=6), and 34 μM (range 6.7 to 71 μM, n=6), respectively.

Resistance:

In Cell Culture

Penciclovir-resistant HSV-1 and HSV-2 strains were isolated in cell culture. Penciclovir-resistant mutants of HSV and VZV resulted from mutations in the viral thymidine kinase (TK) and DNA polymerase (POL) genes. Frameshifts were commonly isolated and result in premature truncation of the HSV TK product with decreased enzymatic activity and consequent decreased susceptibility to penciclovir. Mutations in the viral TK gene may lead to complete loss of TK activity (TK negative), reduced levels of TK activity (TK partial), or alteration in the ability of viral TK to phosphorylate the drug without an equivalent loss in the ability to phosphorylate thymidine (TK altered). In cell culture, the following resistance-associated substitutions in TK of HSV-1 and HSV-2 were observed: HSV-1 TK G6C, F13L, H142Y, G200D, L205S, S254Stop, V267G, and T287M; HSV-2 TK G39E, F191L, E226K, and T288M. The median EC50 values observed in a plaque reduction assay with penciclovir resistant HSV-1, HSV-2, and VZV were 69 μM (range 14 to 115 μM, n=6), 46 μM (range 4 to > 395 μM, n=9), and 92 μM (range 51 to 148 μM, n=4), respectively.

Resistance and Cross-resistance in Clinical Isolates from HSV-Infected Patients

Clinical HSV-1 and HSV-2 isolates obtained from patients who failed treatment with acyclovir for their α-herpesvirus infections were evaluated for genotypic changes in the TK and POL genes. These HSV isolates had frameshift mutations leading to loss of thymidine kinase or had substitutions in the viral thymidine kinase and viral DNA polymerase.

Phenotypic analysis of these clinical isolates confirmed resistance to penciclovir and acyclovir. These and other resistance-associated substitutions reported in the literature, or observed in clinical trials, are listed in Table 6. The list is not all inclusive and additional changes will likely be identified in HSV variants isolated from patients who fail penciclovir containing regimens. The possibility of viral resistance to penciclovir should be considered in patients who fail to respond or experience recurrent viral shedding during therapy.

Table 6: Summary of Known HSV TK and POL Amino Acid Substitutions Conferring Resistance to Acyclovir and Cross-Resistance to Penciclovir

HSV-1 | TK | G6C, R32H, R51W, Y53C/H, H58N, G59W, G61A, S74Stop, E83K, P84L, T103P, Q104Stop, D116N, M121R, I143V, R163H, L170P, Y172C, A174P, R176Q/W, Q185R, A189V, G200D, G206R, L208H, R216C, R220H, R222C/H, FS 224, Y239S, T245M, Q250Stop, S254Stop, R256W, Q261Stop, R281Stop, T287M, L315S, M322K, C336Y
HSV-2 | TK | G39E, R51W, Y53N, R177W*, R221H, T288M*
HSV-1 | POL | A657T, D672N, V715G, A719V, S724N, E798K, V813M, N815S, Y818C, G841S, R842S, F891C, V958L
HSV-2 | POL | -

* These substitutions were also observed in penciclovir-treated patients.

Note: Many additional pathways to penciclovir resistance likely exist.

Cross-resistance has been observed among HSV isolates carrying foscarnet resistance-associated substitutions (Table 7).

Table 7: Summary of Known HSV-1 POL Amino Acid Substitutions Conferring Resistance to Foscarnet and Cross-Resistance to Penciclovir

HSV-1 | POL | D672N, S724N, E798K, V813M, Y818C, F891C, V958L

13 NONCLINICAL TOXICOLOGY

13.1 Carcinogenesis, Mutagenesis, Impairment of Fertility

Carcinogenesis: Two-year dietary carcinogenicity studies with famciclovir were conducted in rats and mice. An increase in the incidence of mammary adenocarcinoma (a common tumor in animals of this strain) was seen in female rats receiving the high dose of 600 mg/kg/day (1.1 to 4.5x the human systemic exposure at the recommended total daily oral dose ranging between 500 mg and 2000 mg, based on area under the plasma concentration curve comparisons [24 hr AUC] for penciclovir). No increases in tumor incidence were reported in male rats treated at doses up to 240 mg/kg/day (0.7 to 2.7x the human AUC), or in male and female mice at doses up to 600 mg/kg/day (0.3 to 1.2x the human AUC).

Mutagenesis: Famciclovir and penciclovir (the active metabolite of famciclovir) were tested for genotoxic potential in a battery of in vitro and in vivo assays. Famciclovir and penciclovir were negative in in vitro tests for gene mutations in bacteria (S. typhimurium and E. coli) and unscheduled DNA synthesis in mammalian HeLa 83 cells (at doses up to 10,000 and 5,000 mcg/plate, respectively). Famciclovir was also negative in the L5178Y mouse lymphoma assay (5000 mcg/mL), the in vivo mouse micronucleus test (4800 mg/kg), and rat dominant lethal study (5000 mg/kg). Famciclovir induced increases in polyploidy in human lymphocytes in vitro in the absence of chromosomal damage (1200 mcg/mL). Penciclovir was positive in the L5178Y mouse lymphoma assay for gene mutation/chromosomal aberrations, with and without metabolic activation (1000 mcg/mL). In human lymphocytes, penciclovir caused chromosomal aberrations in the absence of metabolic activation (250 mcg/mL). Penciclovir caused an increased incidence of micronuclei in mouse bone marrow in vivo when administered intravenously at doses highly toxic to bone marrow (500 mg/kg), but not when administered orally.

Impairment of fertility: Testicular toxicity was observed in rats, mice, and dogs following repeated administration of famciclovir or penciclovir. Testicular changes included atrophy of the seminiferous tubules, reduction in sperm count, and/or increased incidence of sperm with abnormal morphology or reduced motility. The degree of toxicity to male reproduction was related to dose and duration of exposure. In male rats, decreased fertility was observed after 10 weeks of dosing at 500 mg/kg/day (1.4 to 5.7x the human AUC). The no observable effect level for sperm and testicular toxicity in rats following chronic administration (26 weeks) was 50 mg/kg/day (0.15 to 0.6x the human systemic exposure based on AUC comparisons). Testicular toxicity was observed following chronic administration to mice (104 weeks) and dogs (26 weeks) at doses of 600 mg/kg/day (0.3 to 1.2x the human AUC) and 150 mg/kg/day (1.3 to 5.1x the human AUC), respectively.

Famciclovir had no effect on general reproductive performance or fertility in female rats at doses up to 1000 mg/kg/day (2.7 to 10.8x the human AUC).

14 CLINICAL STUDIES

14.1 Herpes Labialis (Cold Sores)

A randomized, double-blind, placebo-controlled trial was conducted in 701 immunocompetent adults with recurrent herpes labialis. Patients self-initiated therapy within 1 hour of first onset of signs or symptoms of a recurrent herpes labialis episode with famciclovir 1500 mg as a single dose (n=227), famciclovir 750 mg twice daily (n=220) or placebo (n=254) for 1 day. The median time to healing among patients with non-aborted lesions (progressing beyond the papule stage) was 4.4 days in the famciclovir 1500 mg single-dose group (n=152) as compared to 6.2 days in the placebo group (n=168). The median difference in time to healing between the placebo and famciclovir 1500 mg treated groups was 1.3 days (95% CI: 0.6 to 2.0). No differences in proportion of patients with aborted lesions (not progressing beyond the papule stage) were observed between patients receiving famciclovir or placebo: 33% for famciclovir 1500 mg single dose and 34% for placebo. The median time to loss of pain and tenderness was 1.7 days in famciclovir 1500 mg single dose-treated patients vs. 2.9 days in placebo-treated patients.

14.2 Genital Herpes

Recurrent episodes: A randomized, double-blind, placebo-controlled trial was conducted in 329 immunocompetent adults with recurrent genital herpes. Patients self-initiated therapy within 6 hours of the first sign or symptom of a recurrent genital herpes episode with either famciclovir 1000 mg twice daily (n=163) or placebo (n=166) for 1 day. The median time to healing among patients with non-aborted lesions (progressing beyond the papule stage) was 4.3 days in famciclovir-treated patients (n=125) as compared to 6.1 days in placebo-treated patients (n=145). The median difference in time to healing between the placebo and famciclovir-treated groups was 1.2 days (95% CI: 0.5 to 2.0). Twenty-three percent of famciclovir-treated patients had aborted lesions (no lesion development beyond erythema) vs. 13% in placebo-treated patients. The median time to loss of all symptoms (e.g., tingling, itching, burning, pain, or tenderness) was 3.3 days in famciclovir-treated patients vs. 5.4 days in placebo-treated patients.

A randomized (2:1), double-blind, placebo-controlled trial was conducted in 304 immunocompetent black and African American adults with recurrent genital herpes. Patients self-initiated therapy within 6 hours of the first sign or symptom of a recurrent genital herpes episode with either famciclovir 1000 mg twice daily (n=206) or placebo (n=98) for 1 day. The median time to healing among patients with non-aborted lesions was 5.4 days in famciclovir-treated patients (n=152) as compared to 4.8 days in placebo-treated patients (n=78). The median difference in time to healing between the placebo and famciclovir-treated groups was -0.26 days (95% CI: -0.98 to 0.40).

Suppressive therapy: Two randomized, double-blind, placebo-controlled, 12-month trials were conducted in 934 immunocompetent adults with a history of 6 or more recurrences of genital herpes episodes per year. Comparisons included famciclovir 125 mg three times daily, 250 mg twice daily, 250 mg three times daily, and placebo. At 12 months, 60% to 65% of patients were still receiving famciclovir and 25% were receiving placebo treatment. Recurrence rates at 6 and 12 months in patients treated with the 250 mg twice daily dose are shown in Table 8.

Table 8: Recurrence Rates at 6 and 12 Months in Adults with Recurrent Genital Herpes on Suppressive Therapy
 | Recurrence Rates; at 6 Months |  | Recurrence Rates; at 12 Months
 | Famciclovir; 250 mg twice daily (n=236) | Placebo; (n=233) | Famciclovir; 250 mg twice daily (n=236) | Placebo; (n=233)
Recurrence-free | 39% | 10% | 29% | 6%
Recurrences [Based on patient reported data; not necessarily confirmed by a physician.] | 47% | 74% | 53% | 78%
Lost to follow-up [Patients recurrence-free at time of last contact prior to withdrawal.] | 14% | 16% | 17% | 16%

Famciclovir-treated patients had approximately one fifth the median number of recurrences as compared to placebo-treated patients. Higher doses of famciclovir were not associated with an increase in efficacy.

14.3 Recurrent Orolabial or Genital Herpes in HIV-Infected Patients

A randomized, double-blind trial compared famciclovir 500 mg twice daily for 7 days (n=150) with oral acyclovir 400 mg 5 times daily for 7 days (n=143) in HIV-infected patients with recurrent orolabial or genital herpes treated within 48 hours of lesion onset. Approximately 40% of patients had a CD4^+ count below 200 cells/mm^3, 54% of patients had anogenital lesions and 35% had orolabial lesions. Famciclovir therapy was comparable to oral acyclovir in reducing new lesion formation and in time to complete healing.

14.4 Herpes Zoster (Shingles)

Two randomized, double-blind trials, 1 placebo-controlled and 1 active-controlled, were conducted in 964 immunocompetent adults with uncomplicated herpes zoster. Treatment was initiated within 72 hours of first lesion appearance and was continued for 7 days.

In the placebo-controlled trial, 419 patients were treated with either famciclovir 500 mg three times daily (n=138), famciclovir 750 mg three times daily (n=135) or placebo (n=146). The median time to full crusting was 5 days among famciclovir 500 mg-treated patients as compared to 7 days in placebo-treated patients. The times to full crusting, loss of vesicles, loss of ulcers, and loss of crusts were shorter for famciclovir 500 mg-treated patients than for placebo-treated patients in the overall study population. The effects of famciclovir were greater when therapy was initiated within 48 hours of rash onset; it was also more profound in patients 50 years of age or older. Among the 65.2% of patients with at least 1 positive viral culture, famciclovir treated patients had a shorter median duration of viral shedding than placebo-treated patients (1 day and 2 days, respectively).

There were no overall differences in the duration of pain before rash healing between famciclovir- and placebo-treated groups. In addition, there was no difference in the incidence of pain after rash healing (postherpetic neuralgia) between the treatment groups. In the 186 patients (44.4% of total study population) who developed postherpetic neuralgia, the median duration of postherpetic neuralgia was shorter in patients treated with famciclovir 500 mg than in those treated with placebo (63 days and 119 days, respectively). No additional efficacy was demonstrated with higher dose of famciclovir.

In the active-controlled trial, 545 patients were treated with 1 of 3 doses of famciclovir three times daily or with acyclovir 800 mg five times daily. Times to full lesion crusting and times to loss of acute pain were comparable for all groups and there were no statistically significant differences in the time to loss of postherpetic neuralgia between famciclovir and acyclovir-treated groups.

16 HOW SUPPLIED/STORAGE AND HANDLING

Famciclovir Tablets are supplied as follows:

125 mg – White, round, film-coated, unscored tablets, debossed with “8117” on one side and “93” on the other side. Available in bottles of 30 (NDC 42291-414-30).

250 mg – White, round, film-coated, unscored tablets, debossed with “8118” on one side and “93” on the other side. Available in bottles of 30 (NDC 42291-415-30).

500 mg – White, capsule-shaped, film-coated, unscored tablets, debossed with “8119” on one side and “93” on the other side. Available in bottles of 30 (NDC 42291-416-30).

Store at 20° to 25°C (68° to 77°F) [See USP Controlled Room Temperature].

Dispense in a tight, light-resistant container as defined in the USP, with a child-resistant closure (as required).

KEEP THIS AND ALL MEDICATIONS OUT OF THE REACH OF CHILDREN.

17 PATIENT COUNSELING INFORMATION

Advise the patient to read the FDA-approved patient labeling (Patient Information).

There is no evidence that famciclovir will affect the ability of a patient to drive or to use machines. However, patients who experience dizziness, somnolence, confusion or other central nervous system disturbances while taking famciclovir should refrain from driving or operating machinery.

Herpes Labialis (Cold Sores)

Patients should be advised to initiate treatment at the earliest sign or symptom of a recurrence of cold sores (e.g., tingling, itching, burning, pain, or lesion). Patients should be instructed that treatment for cold sores should not exceed 1 dose. Patients should be informed that famciclovir is not a cure for cold sores.

Genital Herpes

Patients should be informed that famciclovir is not a cure for genital herpes. There are no data evaluating whether famciclovir will prevent transmission of infection to others. Because genital herpes is a sexually transmitted disease, patients should avoid contact with lesions or intercourse when lesions and/or symptoms are present to avoid infecting partners. Genital herpes is frequently transmitted in the absence of symptoms through asymptomatic viral shedding. Therefore, patients should be counseled to use safer sex practices.

If episodic therapy for recurrent genital herpes is indicated, patients should be advised to initiate therapy at the first sign or symptom of an episode.

There are no data on safety or effectiveness of chronic suppressive therapy of longer than 1-year duration.

Herpes Zoster (Shingles)

There are no data on treatment initiated more than 72 hours after onset of zoster rash. Patients should be advised to initiate treatment as soon as possible after a diagnosis of herpes zoster.

All brand names listed are the registered trademarks of their respective owners and are not trademarks of AvKARE.

Manufactured for:

AvKARE

Pulaski, TN 38478

Mfg. Rev. 12/18

AV 05/21 (P)

PATIENT INFORMATION

Famciclovir (fam SYE klo veer) Tablets

What are famciclovir tablets?

Famciclovir tablets are a prescription antiviral medicine used:

- in adults with a normal immune system to:
  - treat outbreaks of cold sores
  - treat outbreaks of genital herpes
  - decrease the number of outbreaks of genital herpes
  - treat shingles (herpes zoster)
- in adults with human immunodeficiency virus (HIV) to treat outbreaks of herpes in or around the mouth, genitals or anal area

It is not known if famciclovir tablets are safe and effective for:

- the first outbreak of genital herpes
- shingles in the eye(s)
- people with weakened immune systems, other than for the treatment of outbreaks of herpes in people with HIV
- black and African American people with genital herpes outbreaks

It is not known if famciclovir tablets are effective in children.

Do not take famciclovir tablets if you are allergic to any of its ingredients or to Denavir® (penciclovir cream). See the end of this Patient Information leaflet for a complete list of ingredients in famciclovir tablets.

Before you take famciclovir tablets, tell your healthcare provider about all of your medical conditions, including if you:

- have kidney or liver problems
- are pregnant or plan to become pregnant. It is not known if famciclovir tablets will harm your unborn baby.
- are breastfeeding or plan to breastfeed. It is not known if famciclovir passes into your breastmilk or how it may affect your breast fed baby.

Tell your healthcare provider about all the medicines you take, including prescription and over-the-counter medicines, vitamins, and herbal supplements.

How should I take famciclovir tablets?

- Take famciclovir tablets exactly as prescribed by your healthcare provider.
- Your healthcare provider will tell you how many famciclovir tablets to take and when to take them. Your dose of famciclovir tablets and how often you take it may be different depending on your condition.
- Famciclovir tablets may be taken with or without food.
- If you are taking famciclovir tablets for outbreaks of cold sores or genital herpes, take famciclovir tablets as soon as you have the first symptoms of the infection such as itching, redness, pain, burning or tingling, or when the sore appears.
- If you take too many famciclovir tablets, call your healthcare provider or go to the nearest hospital emergency room right away.

What should I avoid while taking famciclovir tablets?

You should avoid driving or operating machinery if you get dizziness, sleepiness or confusion during treatment with famciclovir tablets.

What are the possible side effects of famciclovir tablets?

The most common side effects of famciclovir tablets are headache and nausea.

These are not all the possible side effects of famciclovir tablets.

Call your doctor for medical advice about side effects. You may report side effects to FDA at 1-800-FDA-1088.

How should I store famciclovir tablets?

- Store famciclovir tablets at room temperature between 68° to 77°F (20° to 25°C).

Keep famciclovir tablets and all medicines out of reach from children.

General information about the safe and effective use of famciclovir tablets

Famciclovir tablets are not a cure for cold sores or genital herpes. It is not known if famciclovir tablets can stop the spread of herpes to others.

If you are sexually active, you can pass herpes to your partner even if you are taking famciclovir tablets. Herpes can be passed to your partner even if you do not have active symptoms. You should continue to practice safer sex to lower the chances of spreading genital herpes to others. Do not have sexual contact with your partner during an outbreak of genital herpes or if you have any symptoms of genital herpes. Ask your healthcare provider for more information about safer sex practices.

Medicines are sometimes prescribed for purposes other than those listed in a Patient Information leaflet. Do not use famciclovir tablets for a condition for which it was not prescribed. Do not give famciclovir tablets to other people, even if they have the same symptoms you have. They may harm them. You can ask your healthcare provider or pharmacist for information about famciclovir tablets that is written for health professionals.

What are the ingredients in famciclovir tablets?

Active ingredient: famciclovir

Inactive ingredients: croscarmellose sodium, hydroxypropyl cellulose, hypromellose, polydextrose, polyethylene glycol, silicified microcrystalline cellulose, sodium starch glycolate, sodium stearyl fumarate, titanium dioxide, and triacetin

All brand names listed are the registered trademarks of their respective owners and are not trademarks of Teva Pharmaceuticals USA.

Manufactured for:

AvKARE

Pulaski, TN 38478

Mfg. Rev. 12/18

AV 05/21 (P)

For more information about famciclovir tablets, call 1-855-361-3993.

This Patient Information has been approved by the U.S. Food and Drug Administration.